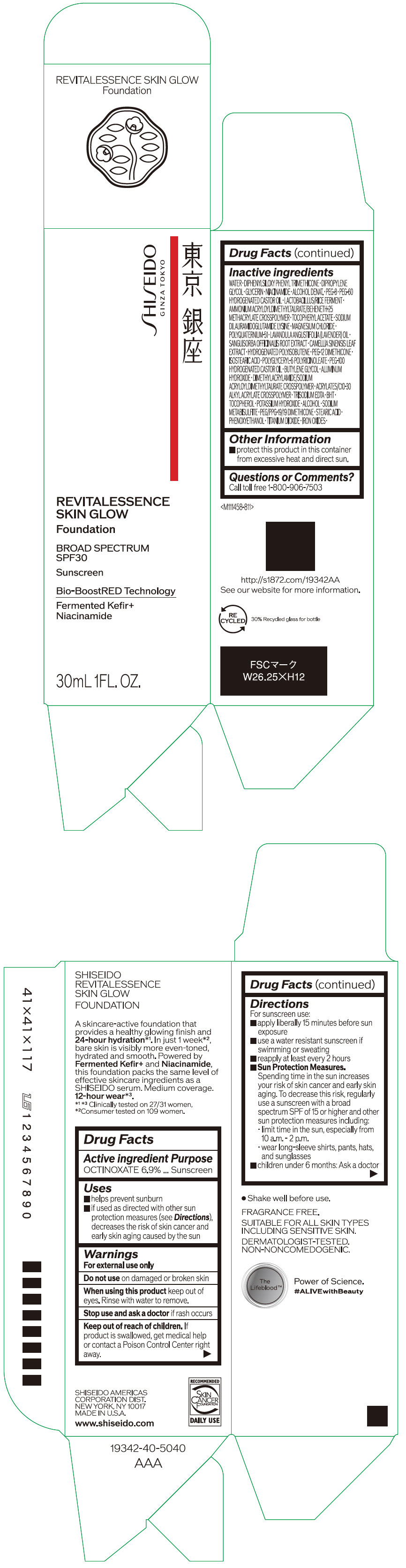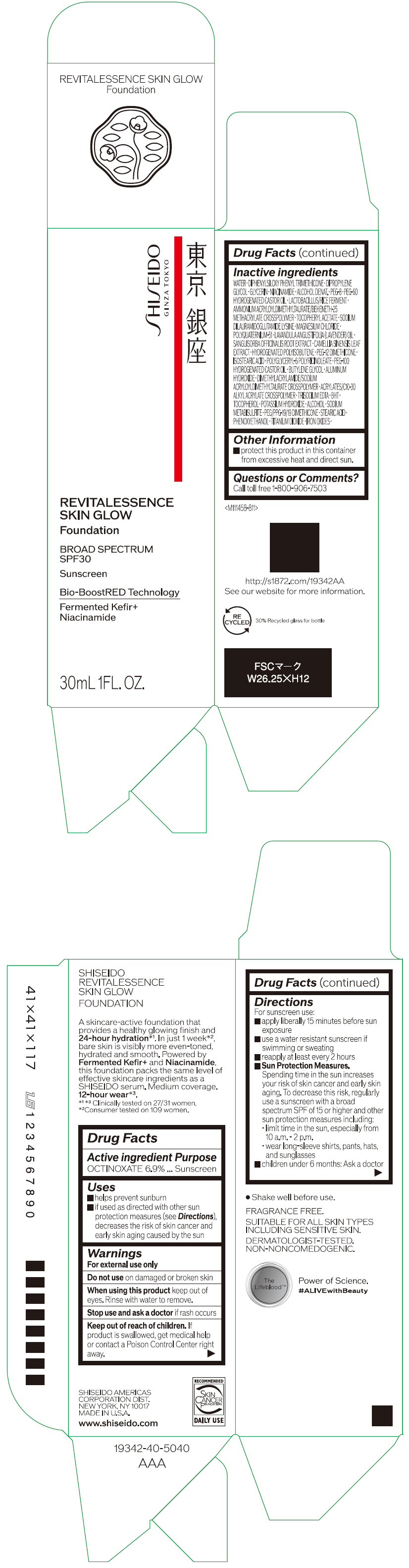 DRUG LABEL: SHISEIDO REVITALESSENCE SKIN GLOW FOUNDATION
NDC: 58411-859 | Form: EMULSION
Manufacturer: SHISEIDO AMERICAS CORPORATION
Category: otc | Type: HUMAN OTC DRUG LABEL
Date: 20250313

ACTIVE INGREDIENTS: OCTINOXATE 2.30805 g/30 mL
INACTIVE INGREDIENTS: WATER; DIPHENYLSILOXY PHENYL TRIMETHICONE; DIPROPYLENE GLYCOL; GLYCERIN; ALCOHOL; NIACINAMIDE; POLYETHYLENE GLYCOL 400; TITANIUM DIOXIDE; FERRIC OXIDE RED; FERRIC OXIDE YELLOW; FERROSOFERRIC OXIDE; PEG-60 HYDROGENATED CASTOR OIL; PEG-12 DIMETHICONE (300 CST); ISOSTEARIC ACID; POLYGLYCERYL-6 POLYRICINOLEATE; PHENOXYETHANOL; BUTYLENE GLYCOL; AMMONIUM ACRYLOYLDIMETHYLTAURATE/BEHENETH-25 METHACRYLATE CROSSPOLYMER (52000 MPA.S); ALUMINUM HYDROXIDE; .ALPHA.-TOCOPHEROL ACETATE, DL-; SODIUM DILAURAMIDOGLUTAMIDE LYSINE; EDETATE TRISODIUM; BUTYLATED HYDROXYTOLUENE; .ALPHA.-TOCOPHEROL; POTASSIUM HYDROXIDE; MAGNESIUM CHLORIDE; SODIUM METABISULFITE; LAVENDER OIL; POLYQUATERNIUM-51 (2-METHACRYLOYLOXYETHYL PHOSPHORYLCHOLINE/N-BUTYL METHACRYLATE; 3:7); SANGUISORBA OFFICINALIS ROOT; GREEN TEA LEAF; PEG/PPG-19/19 DIMETHICONE; HYDROGENATED POLYISOBUTENE (1300 MW); STEARIC ACID

SHISEIDO REVITALESSENCE SKIN GLOW FOUNDATION

Drug Facts

Active ingredients

OCTINOXATE 6.9%

Purpose

Sunscreen

Uses

- helps prevent sunburn
- if used as directed with other sun protection measures (see Directions), decreases the risk of skin cancer and early skin aging caused by the sun

Warnings

For external use only

Do not use on damaged or broken skin

When using this product keep out of eyes. Rinse with water to remove.

Stop use and ask a doctor if rash occurs.

Keep out of reach of children. If product is swallowed, get medical help or contact a Poison Control Center right away.

Directions

For sunscreen use:

- apply liberally 15 minutes before sun exposure
- use a water resistant sunscreen if swimming or sweating
- reapply at least every 2 hours
- Sun Protection Measures. Spending time in the sun increases your risk of skin cancer and early skin aging. To decrease this risk, regularly use a sunscreen with a broad spectrum SPF of 15 or higher and other sun protection measures including:
  - limit time in the sun, especially from 10 a.m. – 2 p.m.
  - wear long-sleeve shirts, pants, hats, and sunglasses
- children under 6 months: Ask a doctor

Inactive Ingredients

WATER･DIPHENYLSILOXY PHENYL TRIMETHICONE･DIPROPYLENE GLYCOL･GLYCERIN･NIACINAMIDE･ALCOHOL DENAT.･PEG-8･PEG-60 HYDROGENATED CASTOR OIL･LACTOBACILLUS/RICE FERMENT･AMMONIUM ACRYLOYLDIMETHYLTAURATE/BEHENETH-25 METHACRYLATE CROSSPOLYMER･TOCOPHERYL ACETATE･SODIUM DILAURAMIDOGLUTAMIDE LYSINE･MAGNESIUM CHLORIDE･POLYQUATERNIUM-51･LAVANDULA ANGUSTIFOLIA (LAVENDER) OIL･SANGUISORBA OFFICINALIS ROOT EXTRACT･CAMELLIA SINENSIS LEAF EXTRACT･HYDROGENATED POLYISOBUTENE･PEG-12 DIMETHICONE･ISOSTEARIC ACID･POLYGLYCERYL-6 POLYRICINOLEATE･PEG-100 HYDROGENATED CASTOR OIL･BUTYLENE GLYCOL･ALUMINUM HYDROXIDE･DIMETHYLACRYLAMIDE/SODIUM ACRYLOYLDIMETHYLTAURATE CROSSPOLYMER･ACRYLATES/C10-30 ALKYL ACRYLATE CROSSPOLYMER･TRISODIUM EDTA･BHT･TOCOPHEROL･POTASSIUM HYDROXIDE･ALCOHOL･SODIUM METABISULFITE･PEG/PPG-19/19 DIMETHICONE･STEARIC ACID･PHENOXYETHANOL･TITANIUM DIOXIDE･IRON OXIDES･

Other information

- protect this product in this container from excessive heat and direct sun.

Questions or comments?

Call toll free 1-800-906-7503

PRINCIPAL DISPLAY PANEL - 30 mL Container Carton - 110

SHISEIDO
GINZA TOKYO

REVITALESSENCE
SKIN GLOW

Foundation

BROAD SPECTRUM
SPF30

Sunscreen

Bio-BoostRED Technology
Fermented Kefir+
Niacinamide

30mL 1FL. OZ.

PRINCIPAL DISPLAY PANEL - 30 mL Container Carton - 120

SHISEIDO
GINZA TOKYO

REVITALESSENCE
SKIN GLOW

Foundation

BROAD SPECTRUM
SPF30

Sunscreen

Bio-BoostRED Technology
Fermented Kefir+
Niacinamide

30mL 1FL. OZ.

PRINCIPAL DISPLAY PANEL - 30 mL Container Carton - 130

SHISEIDO
GINZA TOKYO

REVITALESSENCE
SKIN GLOW

Foundation

BROAD SPECTRUM
SPF30

Sunscreen

Bio-BoostRED Technology
Fermented Kefir+
Niacinamide

30mL 1FL. OZ.

PRINCIPAL DISPLAY PANEL - 30 mL Container Carton - 140

SHISEIDO
GINZA TOKYO

REVITALESSENCE
SKIN GLOW

Foundation

BROAD SPECTRUM
SPF30

Sunscreen

Bio-BoostRED Technology
Fermented Kefir+
Niacinamide

30mL 1FL. OZ.

PRINCIPAL DISPLAY PANEL - 30 mL Container Carton - 150

SHISEIDO
GINZA TOKYO

REVITALESSENCE
SKIN GLOW

Foundation

BROAD SPECTRUM
SPF30

Sunscreen

Bio-BoostRED Technology
Fermented Kefir+
Niacinamide

30mL 1FL. OZ.

PRINCIPAL DISPLAY PANEL - 30 mL Container Carton - 160

SHISEIDO
GINZA TOKYO

REVITALESSENCE
SKIN GLOW

Foundation

BROAD SPECTRUM
SPF30

Sunscreen

Bio-BoostRED Technology
Fermented Kefir+
Niacinamide

30mL 1FL. OZ.

PRINCIPAL DISPLAY PANEL - 30 mL Container Carton - 210

SHISEIDO
GINZA TOKYO

REVITALESSENCE
SKIN GLOW

Foundation

BROAD SPECTRUM
SPF30

Sunscreen

Bio-BoostRED Technology
Fermented Kefir+
Niacinamide

30mL 1FL. OZ.

PRINCIPAL DISPLAY PANEL - 30 mL Container Carton - 220

SHISEIDO
GINZA TOKYO

REVITALESSENCE
SKIN GLOW

Foundation

BROAD SPECTRUM
SPF30

Sunscreen

Bio-BoostRED Technology
Fermented Kefir+
Niacinamide

30mL 1FL. OZ.

PRINCIPAL DISPLAY PANEL - 30 mL Container Carton - 230

SHISEIDO
GINZA TOKYO

REVITALESSENCE
SKIN GLOW

Foundation

BROAD SPECTRUM
SPF30

Sunscreen

Bio-BoostRED Technology
Fermented Kefir+
Niacinamide

30mL 1FL. OZ.

PRINCIPAL DISPLAY PANEL - 30 mL Container Carton - 240

SHISEIDO
GINZA TOKYO

REVITALESSENCE
SKIN GLOW

Foundation

BROAD SPECTRUM
SPF30

Sunscreen

Bio-BoostRED Technology
Fermented Kefir+
Niacinamide

30mL 1FL. OZ.

PRINCIPAL DISPLAY PANEL - 30 mL Container Carton - 250

SHISEIDO
GINZA TOKYO

REVITALESSENCE
SKIN GLOW

Foundation

BROAD SPECTRUM
SPF30

Sunscreen

Bio-BoostRED Technology
Fermented Kefir+
Niacinamide

30mL 1FL. OZ.

PRINCIPAL DISPLAY PANEL - 30 mL Container Carton - 260

SHISEIDO
GINZA TOKYO

REVITALESSENCE
SKIN GLOW

Foundation

BROAD SPECTRUM
SPF30

Sunscreen

Bio-BoostRED Technology
Fermented Kefir+
Niacinamide

30mL 1FL. OZ.

PRINCIPAL DISPLAY PANEL - 30 mL Container Carton - 310

SHISEIDO
GINZA TOKYO

REVITALESSENCE
SKIN GLOW

Foundation

BROAD SPECTRUM
SPF30

Sunscreen

Bio-BoostRED Technology
Fermented Kefir+
Niacinamide

30mL 1FL. OZ.

PRINCIPAL DISPLAY PANEL - 30 mL Container Carton - 320

SHISEIDO
GINZA TOKYO

REVITALESSENCE
SKIN GLOW

Foundation

BROAD SPECTRUM
SPF30

Sunscreen

Bio-BoostRED Technology
Fermented Kefir+
Niacinamide

30mL 1FL. OZ.

PRINCIPAL DISPLAY PANEL - 30 mL Container Carton - 330

SHISEIDO
GINZA TOKYO

REVITALESSENCE
SKIN GLOW

Foundation

BROAD SPECTRUM
SPF30

Sunscreen

Bio-BoostRED Technology
Fermented Kefir+
Niacinamide

30mL 1FL. OZ.

PRINCIPAL DISPLAY PANEL - 30 mL Container Carton - 340

SHISEIDO
GINZA TOKYO

REVITALESSENCE
SKIN GLOW

Foundation

BROAD SPECTRUM
SPF30

Sunscreen

Bio-BoostRED Technology
Fermented Kefir+
Niacinamide

30mL 1FL. OZ.

PRINCIPAL DISPLAY PANEL - 30 mL Container Carton - 350

SHISEIDO
GINZA TOKYO

REVITALESSENCE
SKIN GLOW

Foundation

BROAD SPECTRUM
SPF30

Sunscreen

Bio-BoostRED Technology
Fermented Kefir+
Niacinamide

30mL 1FL. OZ.

PRINCIPAL DISPLAY PANEL - 30 mL Container Carton - 360

SHISEIDO
GINZA TOKYO

REVITALESSENCE
SKIN GLOW

Foundation

BROAD SPECTRUM
SPF30

Sunscreen

Bio-BoostRED Technology
Fermented Kefir+
Niacinamide

30mL 1FL. OZ.

PRINCIPAL DISPLAY PANEL - 30 mL Container Carton - 410

SHISEIDO
GINZA TOKYO

REVITALESSENCE
SKIN GLOW

Foundation

BROAD SPECTRUM
SPF30

Sunscreen

Bio-BoostRED Technology
Fermented Kefir+
Niacinamide

30mL 1FL. OZ.

PRINCIPAL DISPLAY PANEL - 30 mL Container Carton - 420

SHISEIDO
GINZA TOKYO

REVITALESSENCE
SKIN GLOW

Foundation

BROAD SPECTRUM
SPF30

Sunscreen

Bio-BoostRED Technology
Fermented Kefir+
Niacinamide

30mL 1FL. OZ.

PRINCIPAL DISPLAY PANEL - 30 mL Container Carton - 430

SHISEIDO
GINZA TOKYO

REVITALESSENCE
SKIN GLOW

Foundation

BROAD SPECTRUM
SPF30

Sunscreen

Bio-BoostRED Technology
Fermented Kefir+
Niacinamide

30mL 1FL. OZ.

PRINCIPAL DISPLAY PANEL - 30 mL Container Carton - 440

SHISEIDO
GINZA TOKYO

REVITALESSENCE
SKIN GLOW

Foundation

BROAD SPECTRUM
SPF30

Sunscreen

Bio-BoostRED Technology
Fermented Kefir+
Niacinamide

30mL 1FL. OZ.

PRINCIPAL DISPLAY PANEL - 30 mL Container Carton - 450

SHISEIDO
GINZA TOKYO

REVITALESSENCE
SKIN GLOW

Foundation

BROAD SPECTRUM
SPF30

Sunscreen

Bio-BoostRED Technology
Fermented Kefir+
Niacinamide

30mL 1FL. OZ.

PRINCIPAL DISPLAY PANEL - 30 mL Container Carton - 460

SHISEIDO
GINZA TOKYO

REVITALESSENCE
SKIN GLOW

Foundation

BROAD SPECTRUM
SPF30

Sunscreen

Bio-BoostRED Technology
Fermented Kefir+
Niacinamide

30mL 1FL. OZ.

PRINCIPAL DISPLAY PANEL - 30 mL Container Carton - 510

SHISEIDO
GINZA TOKYO

REVITALESSENCE
SKIN GLOW

Foundation

BROAD SPECTRUM
SPF30

Sunscreen

Bio-BoostRED Technology
Fermented Kefir+
Niacinamide

30mL 1FL. OZ.

PRINCIPAL DISPLAY PANEL - 30 mL Container Carton - 520

SHISEIDO
GINZA TOKYO

REVITALESSENCE
SKIN GLOW

Foundation

BROAD SPECTRUM
SPF30

Sunscreen

Bio-BoostRED Technology
Fermented Kefir+
Niacinamide

30mL 1FL. OZ.

PRINCIPAL DISPLAY PANEL - 30 mL Container Carton - 530

SHISEIDO
GINZA TOKYO

REVITALESSENCE
SKIN GLOW

Foundation

BROAD SPECTRUM
SPF30

Sunscreen

Bio-BoostRED Technology
Fermented Kefir+
Niacinamide

30mL 1FL. OZ.

PRINCIPAL DISPLAY PANEL - 30 mL Container Carton - 540

SHISEIDO
GINZA TOKYO

REVITALESSENCE
SKIN GLOW

Foundation

BROAD SPECTRUM
SPF30

Sunscreen

Bio-BoostRED Technology
Fermented Kefir+
Niacinamide

30mL 1FL. OZ.

PRINCIPAL DISPLAY PANEL - 30 mL Container Carton - 550

SHISEIDO
GINZA TOKYO

REVITALESSENCE
SKIN GLOW

Foundation

BROAD SPECTRUM
SPF30

Sunscreen

Bio-BoostRED Technology
Fermented Kefir+
Niacinamide

30mL 1FL. OZ.

PRINCIPAL DISPLAY PANEL - 30 mL Container Carton - 560

SHISEIDO
GINZA TOKYO

REVITALESSENCE
SKIN GLOW

Foundation

BROAD SPECTRUM
SPF30

Sunscreen

Bio-BoostRED Technology
Fermented Kefir+
Niacinamide

30mL 1FL. OZ.